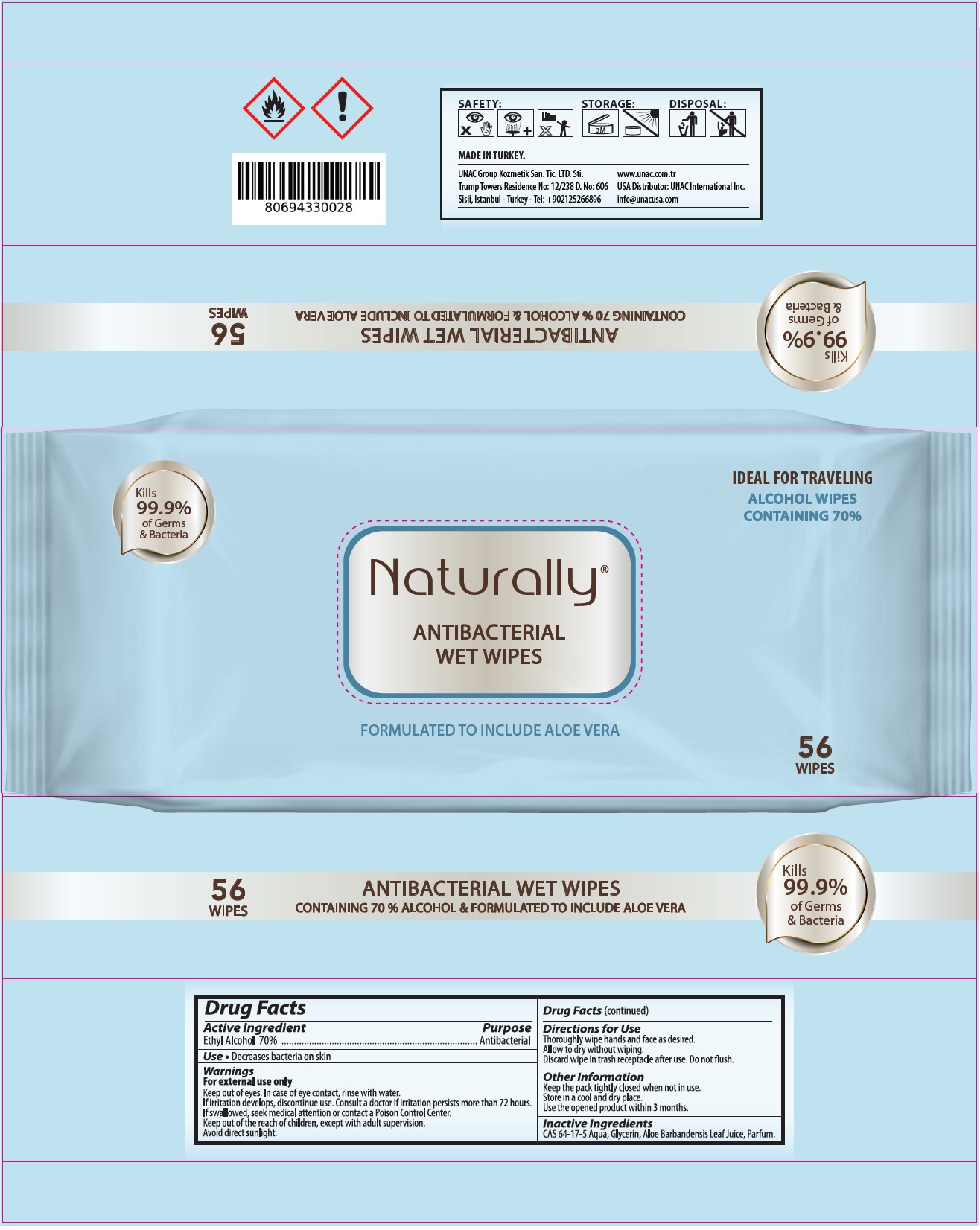 DRUG LABEL: NATURALLY ANTIBACTERIAL WET WIPES
NDC: 74955-040 | Form: CLOTH
Manufacturer: COSMOLIVE KOZMETIK SANAYI VE TICARET ANONIM SIRKETI
Category: otc | Type: HUMAN OTC DRUG LABEL
Date: 20201221

ACTIVE INGREDIENTS: ALCOHOL 70 mL/100 mL
INACTIVE INGREDIENTS: WATER; GLYCERIN; ALOE VERA LEAF

Naturally® ANTIBACTERIAL WET WIPES

Active Ingredient

Ethyl Alcohol 70%

Purpose

Antibacterial

Use

• Decreases bacteria on skin

Warnings

For external use only

Keep out of eyes. In case of eye contact, rinse with water.

If irritation develops, discontinue use. Consult a doctor if irritation persists more than 72 hours.

If swallowed, seek medical attention or contact a Poison Control Center.

Avoid direct sunlight.

KEEP OUT OF REACH OF CHILDREN

Keep out of the reach of children, except with adult supervision.

Directions for Use

Thoroughly wipe hands and face as desired.

Allow to dry without wiping.

Discard wipe in trash receptacle after use. Do not flush.

Other Information

Keep the pack tightly closed when not in use.

Store in a cool and dry place.

Use the opened product within 3 months.

Inactive Ingredients

CAS 64-17-5 Aqua, Glycerin, Aloe Barbadensis Leaf Juice, Parfum.

Kills 99.9% of Germs & Bacteria

IDEAL FOR TRAVELING

ALCOHOL WIPES

CONTAINING 70 % ALCOHOL & FORMULATED TO INCLUDE ALOE VERA

MADE IN TURKEY.

UNAC Group Kozmetik San. Tic. LTD. Sti.
Trump Towers Residence No: 12/238 D. No: 606
Sisli, Istanbul - Turkey - Tel: +902125266896
www.unac.com.tr
USA Distributor: UNAC International Inc.
info@unacusa.com